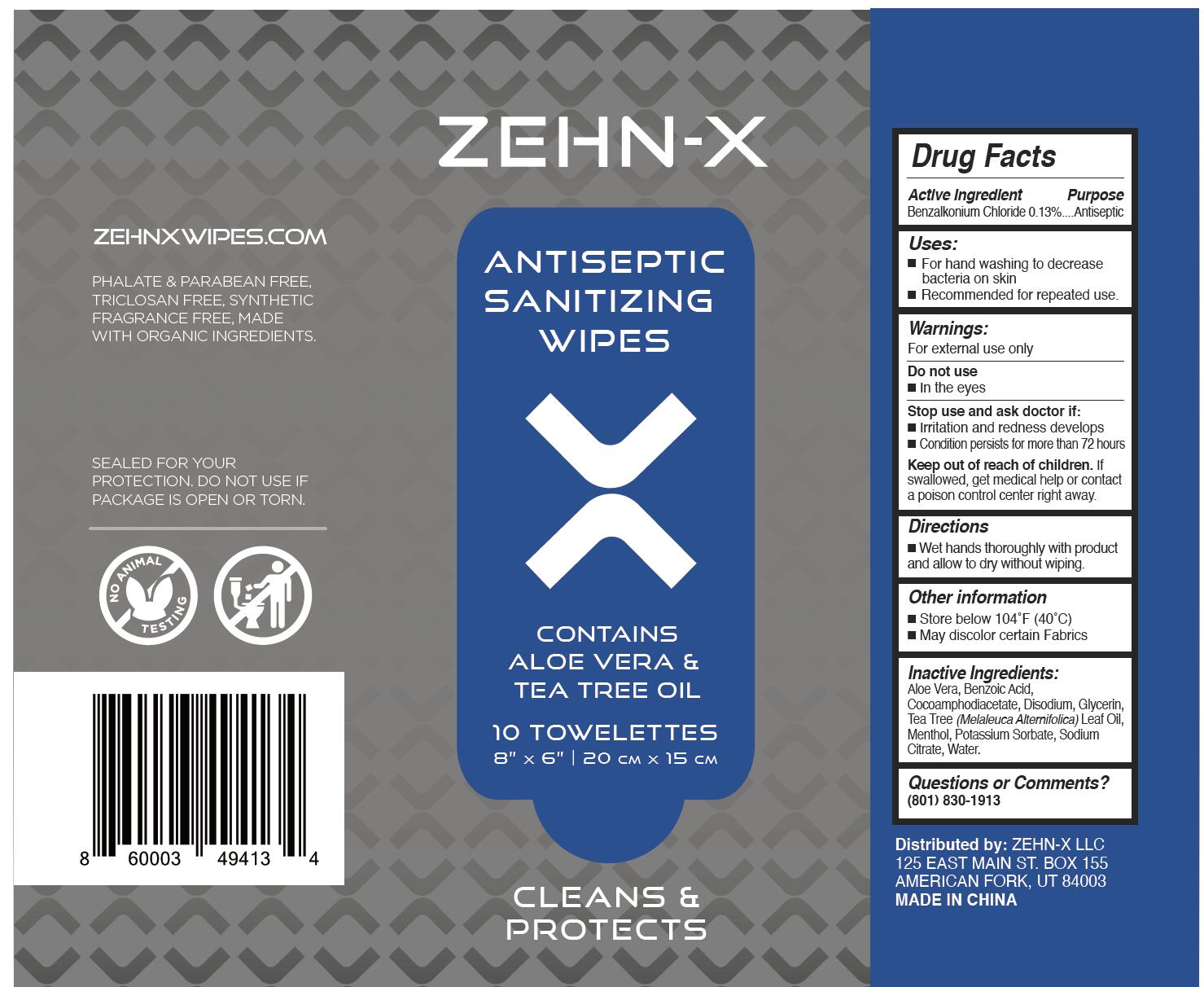 DRUG LABEL: Anitiseptic Sanitizing Wipes
NDC: 78601-002 | Form: CLOTH
Manufacturer: Jiaxing Qinya Sanitary Products Co., Ltd.
Category: otc | Type: HUMAN OTC DRUG LABEL
Date: 20200920

ACTIVE INGREDIENTS: BENZALKONIUM CHLORIDE 0.13 g/100 g
INACTIVE INGREDIENTS: MENTHOL; BENZOIC ACID; DISODIUM COCOAMPHODIACETATE; WATER; TEA TREE OIL; GLYCERIN; ALOE VERA LEAF; SODIUM CITRATE; POTASSIUM SORBATE

78601-002 antiseptic sanitizing wipes 0.13% BENZALKONIUM CHLORIDE

Active Ingredient

Benzalkonium Chloride 0.13%

Purpose

Antiseptic

USE

For hand washing to decrease
bacteria on skin
Recommended for repeated use.

Warning

For external use only
Do not use
■Intheeyes.
Stop use and ask doctor if:
Irritation and redness develops
■Condition persists for more than 72 hours

Keep out of reach of children. If
swallowed, get medical help or contact
a poison control center right away.

Directions

■Wet hands thoroughly with product
and allow to dry without wiping.

Inactive ingredients

Aloe Vera, Benzoic Acid,
Cocoamphodiacetate, Disodium, Glycerin,
Tea Tree (Melaleuca Alternifolica) Leaf Oil,
Menthol, Potassium Sorbate, Sodium
Citrate, Water.